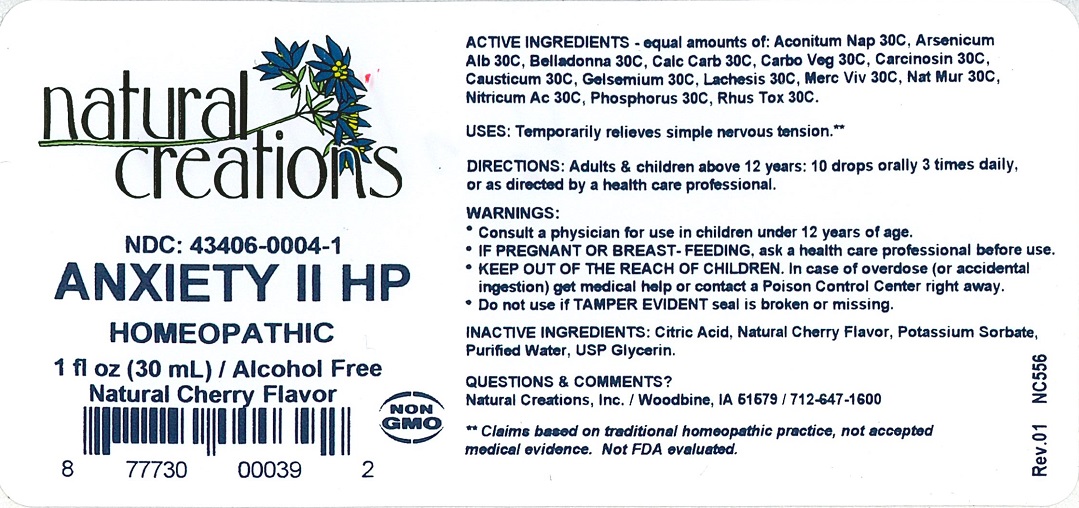 DRUG LABEL: ANXIETY II HP
NDC: 43406-0004 | Form: LIQUID
Manufacturer: Natural Creations, Inc.
Category: homeopathic | Type: HUMAN OTC DRUG LABEL
Date: 20251113

ACTIVE INGREDIENTS: ACONITUM NAPELLUS WHOLE 30 [hp_C]/1 mL; ARSENIC TRIOXIDE 30 [hp_C]/1 mL; ATROPA BELLADONNA 30 [hp_C]/1 mL; OYSTER SHELL CALCIUM CARBONATE, CRUDE 30 [hp_C]/1 mL; ACTIVATED CHARCOAL 30 [hp_C]/1 mL; HUMAN BREAST TUMOR CELL 30 [hp_C]/1 mL; CAUSTICUM 30 [hp_C]/1 mL; GELSEMIUM SEMPERVIRENS ROOT 30 [hp_C]/1 mL; LACHESIS MUTA VENOM 30 [hp_C]/1 mL; MERCURY 30 [hp_C]/1 mL; NITRIC ACID 30 [hp_C]/1 mL; PHOSPHORUS 30 [hp_C]/1 mL; TOXICODENDRON PUBESCENS LEAF 30 [hp_C]/1 mL; SODIUM CHLORIDE 30 [hp_C]/1 mL
INACTIVE INGREDIENTS: CITRIC ACID ACETATE; POTASSIUM SORBATE; water; GLYCERIN

ANXIETY II HP

ACTIVE INGREDIENT

Active Ingredients (HPUS*): Aconitum Napellus 30C, Arsenicum Album 30C, Belladonna 30C, Calcarea Carbonica 30C, Carbo Vegetabilis 30C, Carcinosin 30C, Causticum 30C, Gelsemium 30C, Lachesis Mutus 30C, Mercurius Vivus 30C, Natrum Muriaticum, Nitricum Ac 30C, Phosphorus, Rhus Tox 30C

PURPOSE

USES: Temporarily relieves simple nervous tension.**

INDICATIONS AND USAGE

USES: Temporarly relieves simple nervous tension.**

DOSAGE AND ADMINISTRATION

DIECTIONS: Adults & children above 12 years: 10 drops orally 3 times daily, or as directed by a health care professional.

KEEP OUT OF REACH OF CHILDREN

KEEP OUT OF THE REACH OF CHILDREN. In case of overdose (or accidential ingestion) get medical help or contact a Poison Control Center right away.

WARNINGS:

- Consult a physician for use in chlidren under 12 years of age.
- IF PRAGNANT OR BREAST-FEEDING, ask a health care professional before use.
- KEEP OUT OF THE REACH OF CHILDREN. In case of overdose (or accidential ingestion) get medical help or contact a Poison Control Center right away.
- Do not use if TAMPER EVIDENT seal is broken or missing.

INACTIVE INGREDIENT

Inactive Ingredients: Citric Acid, Natural Cherry Flavor, Potassium Sorbate, Purified Water, USP Glycerin.

QUESTIONS

Ouestions & Comments?

Natural Creations, Inc. / Woodbine, IA 51579 / 712-647-1600

PACKAGE LABEL

NDC:43406-0004-1

ANXIETY II HP

HOMEOPATHIC

1 fl oz (30 mL)

UPC: 877730000392